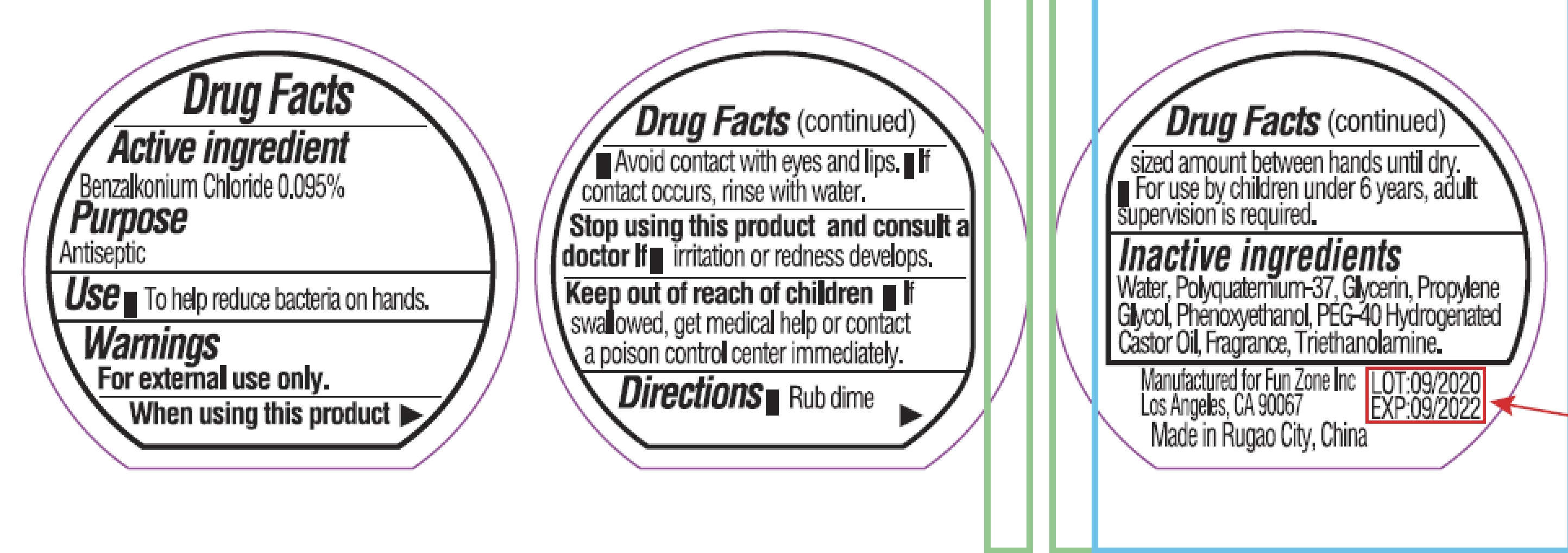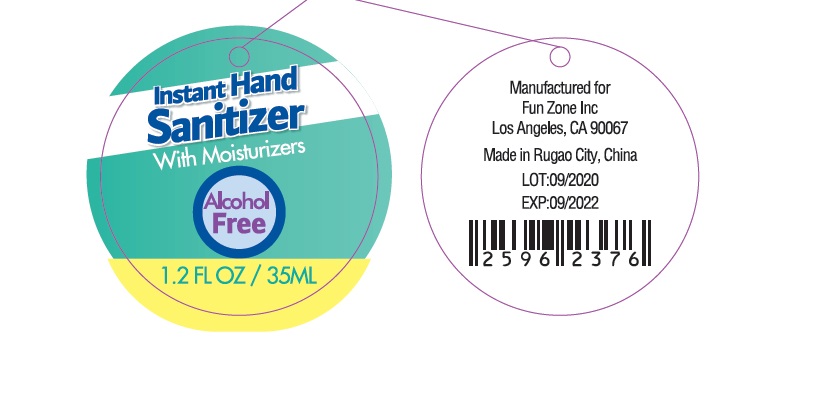 DRUG LABEL: Instant Hand Sanitizer
NDC: 69583-035 | Form: GEL
Manufacturer: Fun Zone, Inc.
Category: otc | Type: HUMAN OTC DRUG LABEL
Date: 20200905

ACTIVE INGREDIENTS: BENZALKONIUM CHLORIDE 0.95 mg/1 mL
INACTIVE INGREDIENTS: PHENOXYETHANOL; POLYQUATERNIUM-37 (10000 MPA.S); POLYOXYL 40 HYDROGENATED CASTOR OIL; TROLAMINE; WATER; GLYCERIN; PROPYLENE GLYCOL

Instant Hand Sanitizer 1.2oz

Active ingredient

Benzalkonium Chloride 0.095%

Purpose

Antiseptic

Use

To help reduce bacteria on hands.

Warnings

For external use only.

When using this product

- Avoid contact with eyes and lips.
- If contact occurs, rinse with water.

Stop using this product and consult a doctor If

irritation or redness develops.

Keep out of reach of children

If swallowed, get medical help or contact a poison control center immediately.

Directions

- Rub dime sized amount between hands until dry.
- For use by children under 6 years, adult supervision is required.

Inactive ingredients

Water, Polyquaternium-37, Glycerin, Propylene Glycol, Phenoxyethanol, PEG-40 Hydrogenated Castor Oil, Fragrance, Triethanolamine.